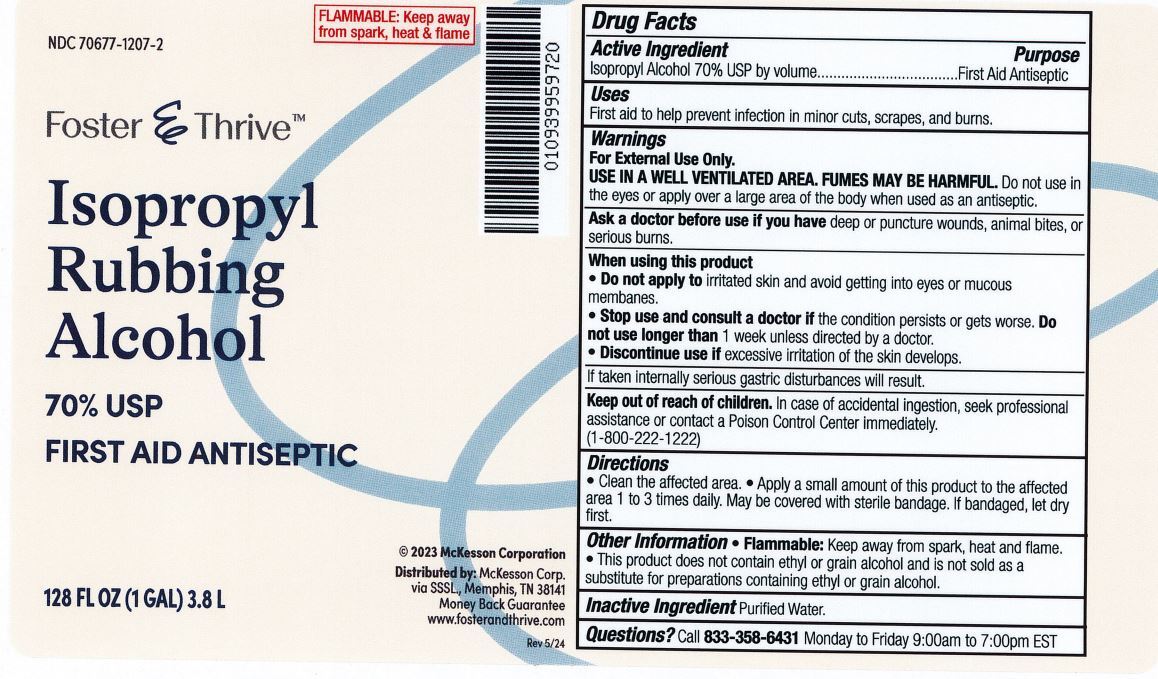 DRUG LABEL: Isopropyl Rubbing Alcohol
NDC: 70677-1207 | Form: LIQUID
Manufacturer: Strategic Sourcing Services LLC
Category: otc | Type: HUMAN OTC DRUG LABEL
Date: 20240914

ACTIVE INGREDIENTS: ISOPROPYL ALCOHOL 70 L/100 L
INACTIVE INGREDIENTS: WATER

Foster & Thrive Isopropyl Alcohol 70% USP

Active Ingredient

Isopropyl Alcohol 70% U.S.P. by volume

Purpose

First Aid Antiseptic

Uses

First aid to help prevent infection in minor cuts, scrapes, and burns.

Warnings

For External use only.

USE IN WELL VENTILATED AREA. FUMES MAY BE HARMFUL.

Do not use

in the eyes or apply over a large area of the body when used as an antiseptic.

In case of

deep or puncture wounds, animal bites, or serious burns, consult a doctor.

When using this product:

- Do not apply to irritated skin and avoid getting into eyes or mucous membranes.

Stop use and consult a doctor

- if the condition persists or gets worse. Do not use longer than 1 week unless directed by a doctor.
- Discontinue use if excessive irritation of the skin develops.

Keep out of reach of children.

In case of accidental overdose, seek professional assistance or contact a Poison Control Center immediately. (1-800-222-1222)

Directions

For antiseptic use: Apply a small amount of this product to the affected area 1 to 3 times daily. May be covered with sterile bandage. If bandaged let dry first.

For rubbing or massage use: Apply compound externally on body until liquid has been absorbed or has been evaporated.

Inactive Ingredient:

Purified Water

Other Information:

FLAMMABLE: Keep away from spark, heat and flame.

NOTICE: This product does not contain eithyl or grain alcohol and is not sold as a substitute for preparations containing ethyl or grain alcohol.